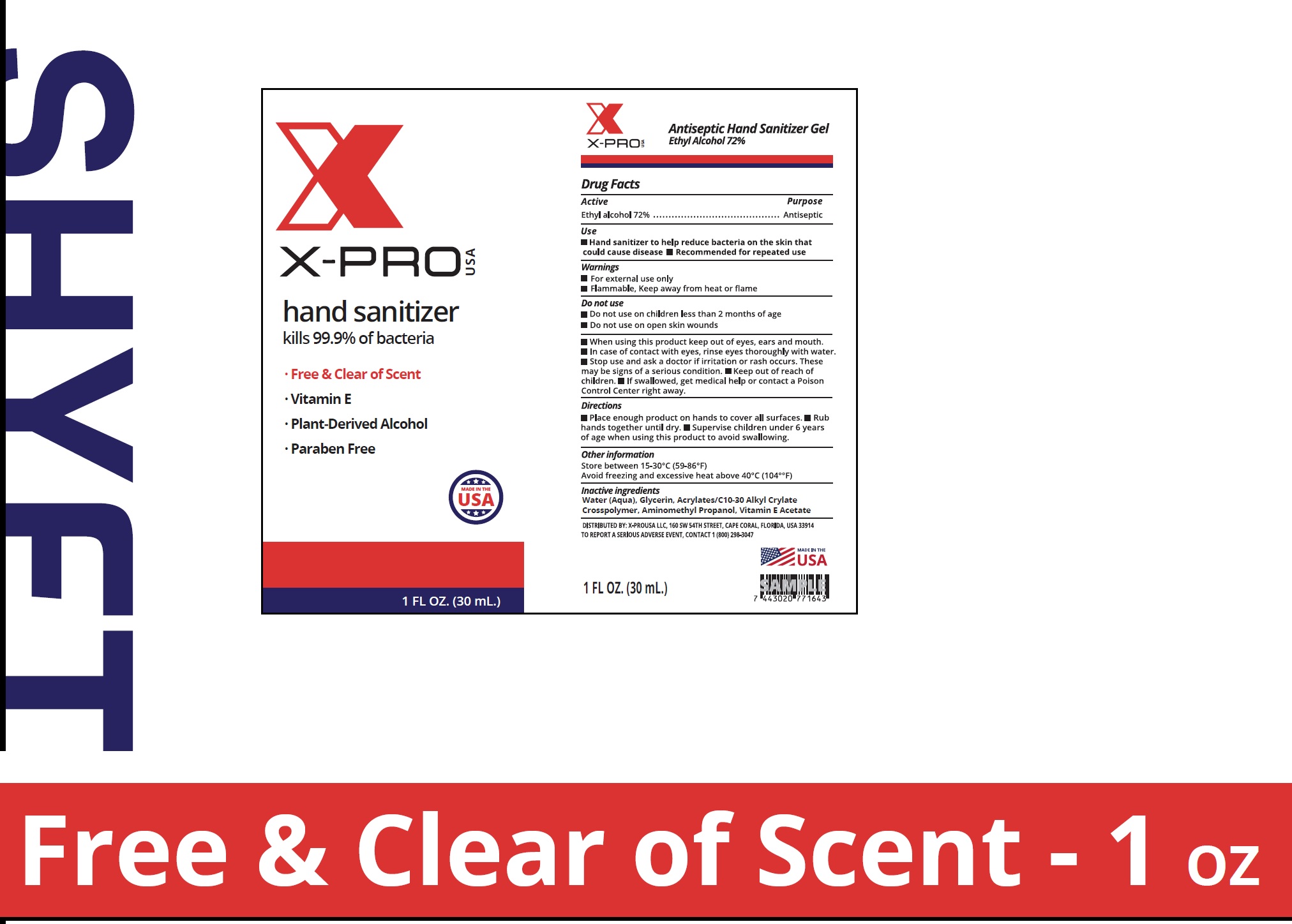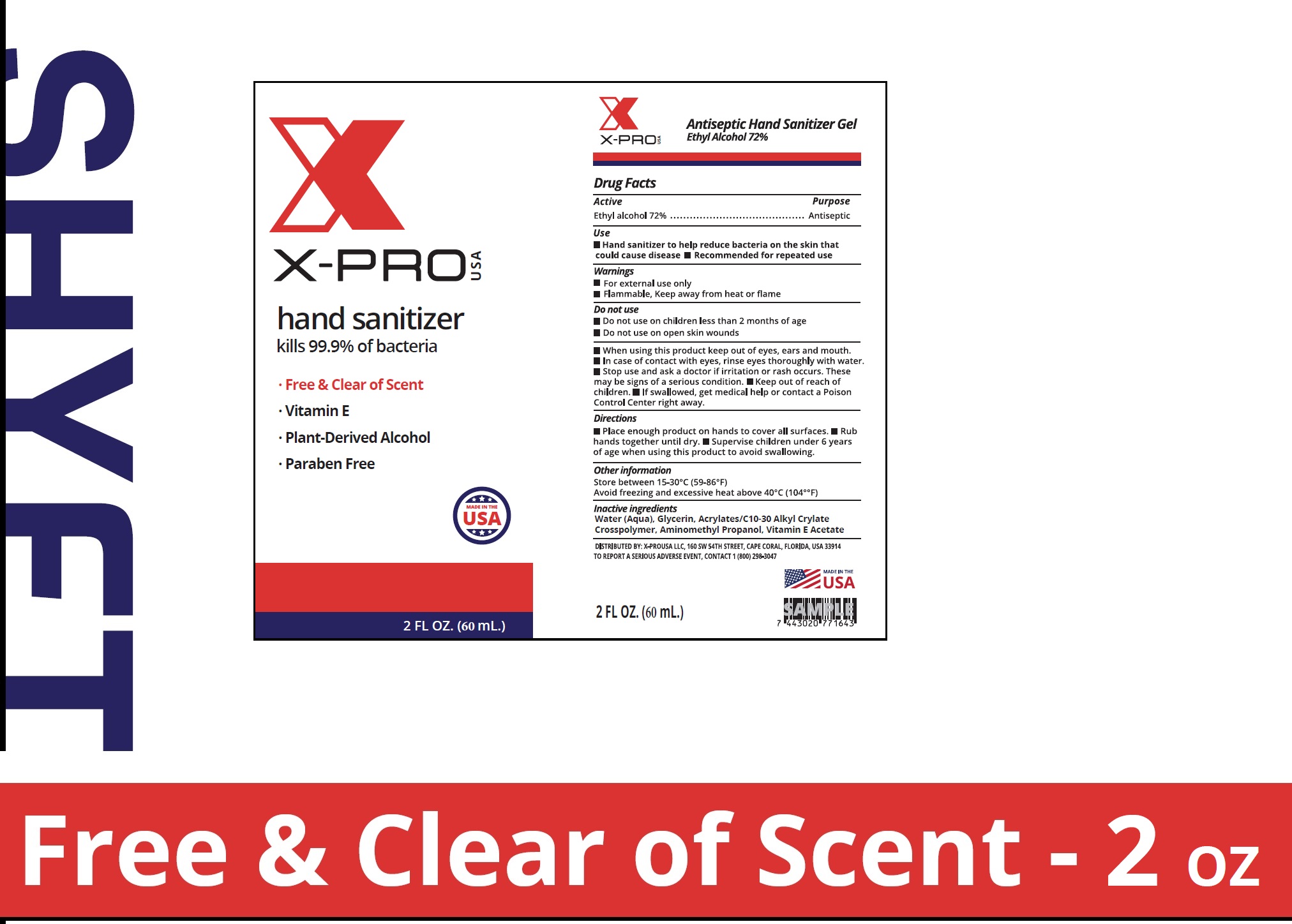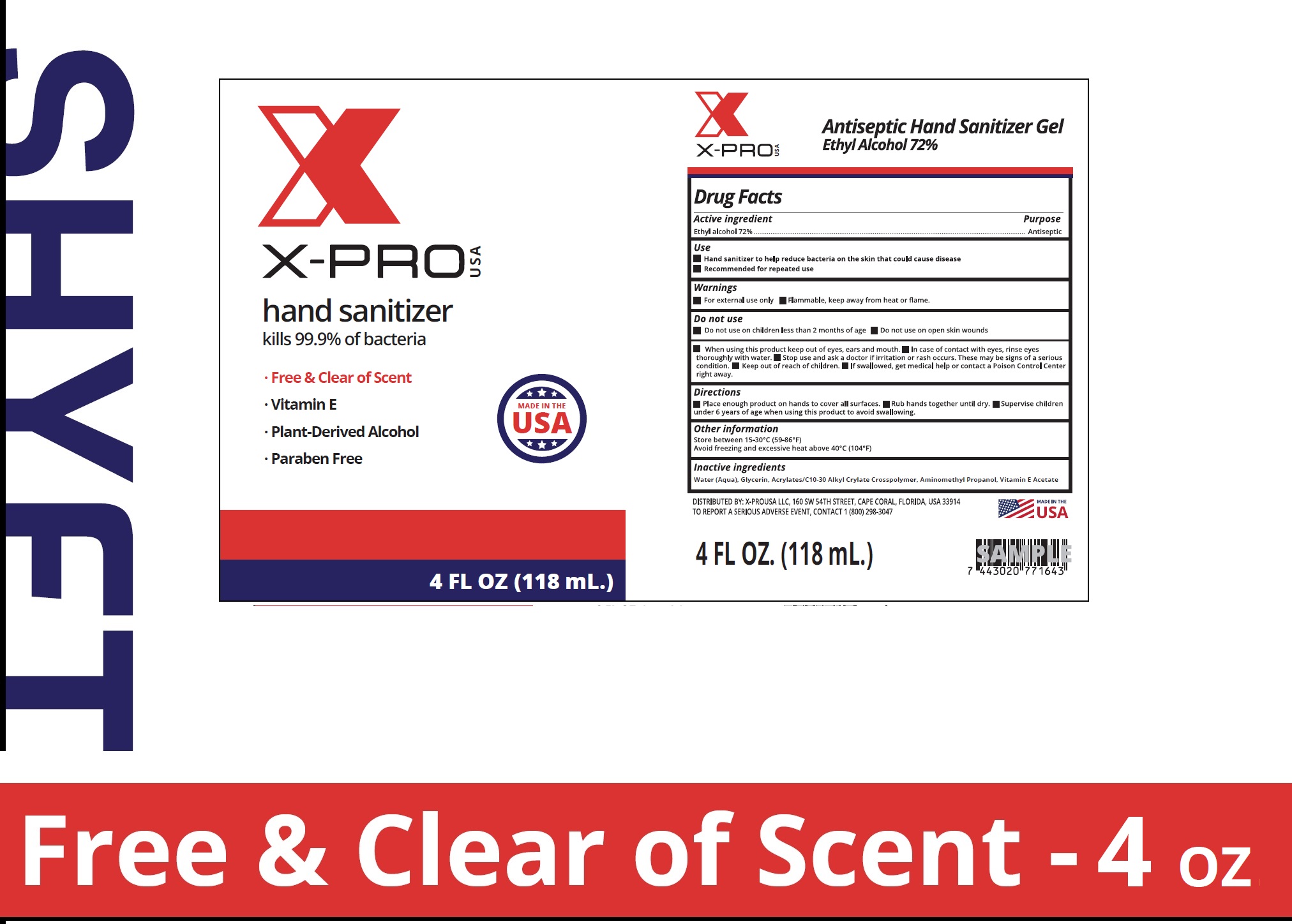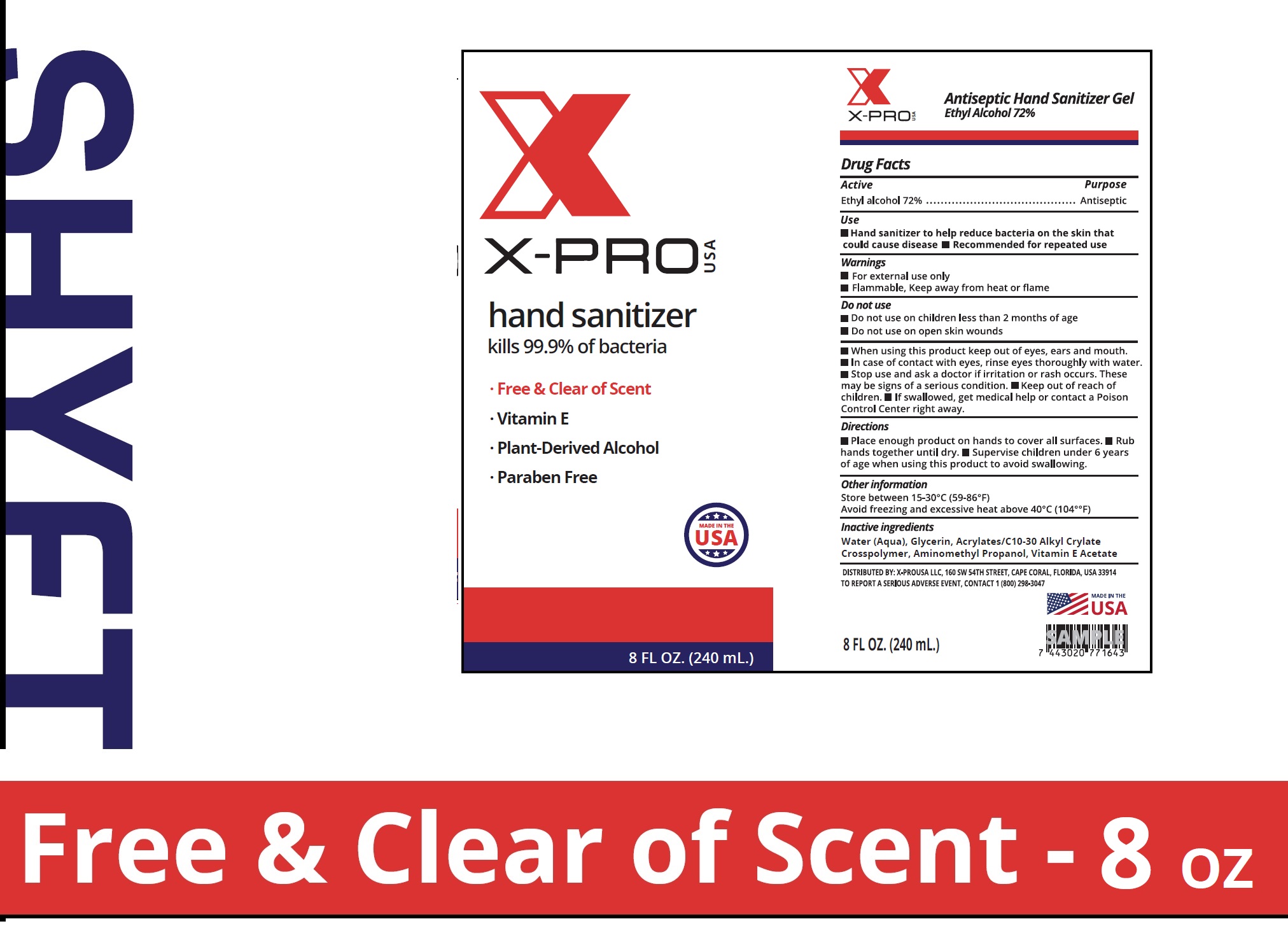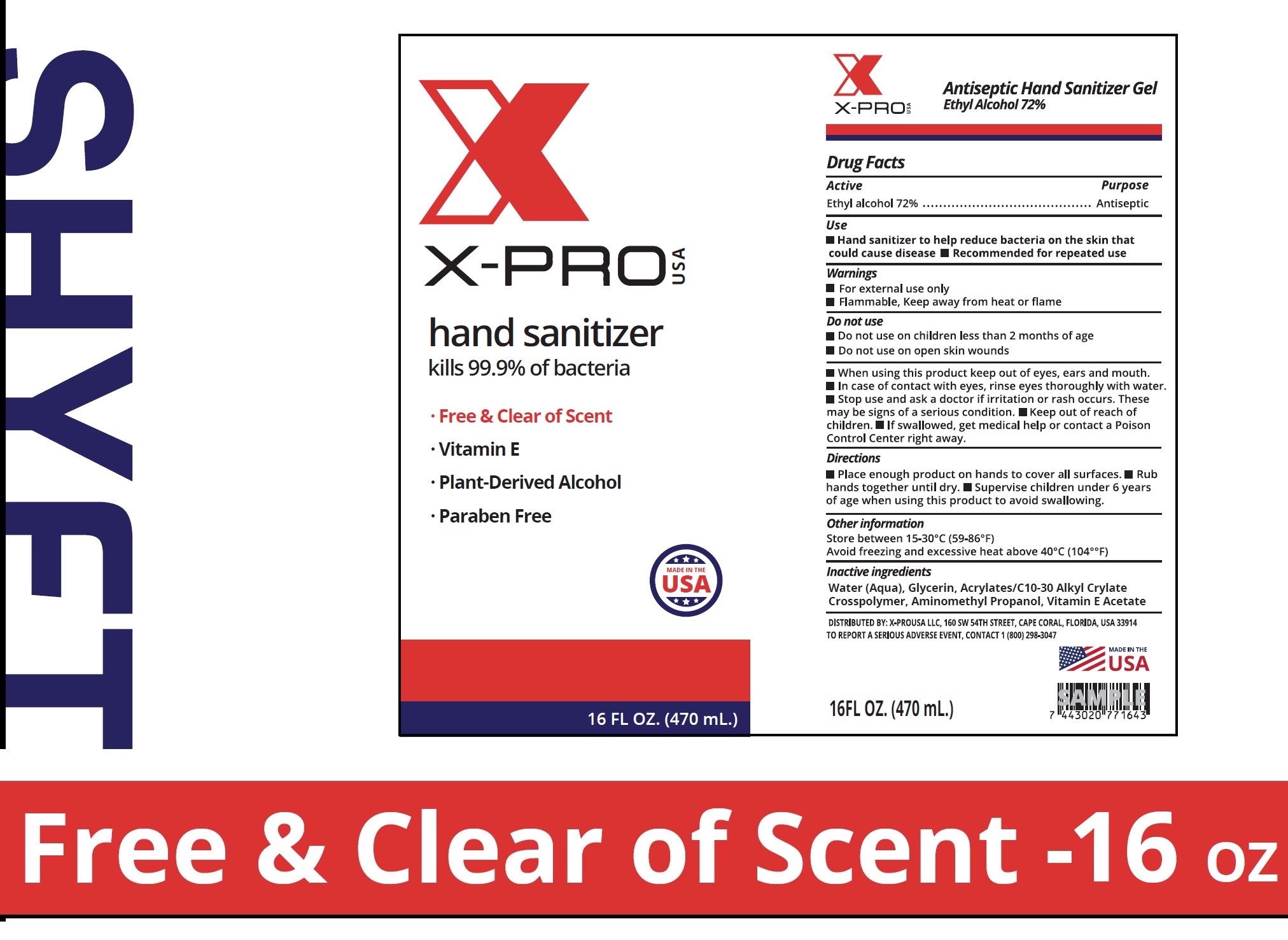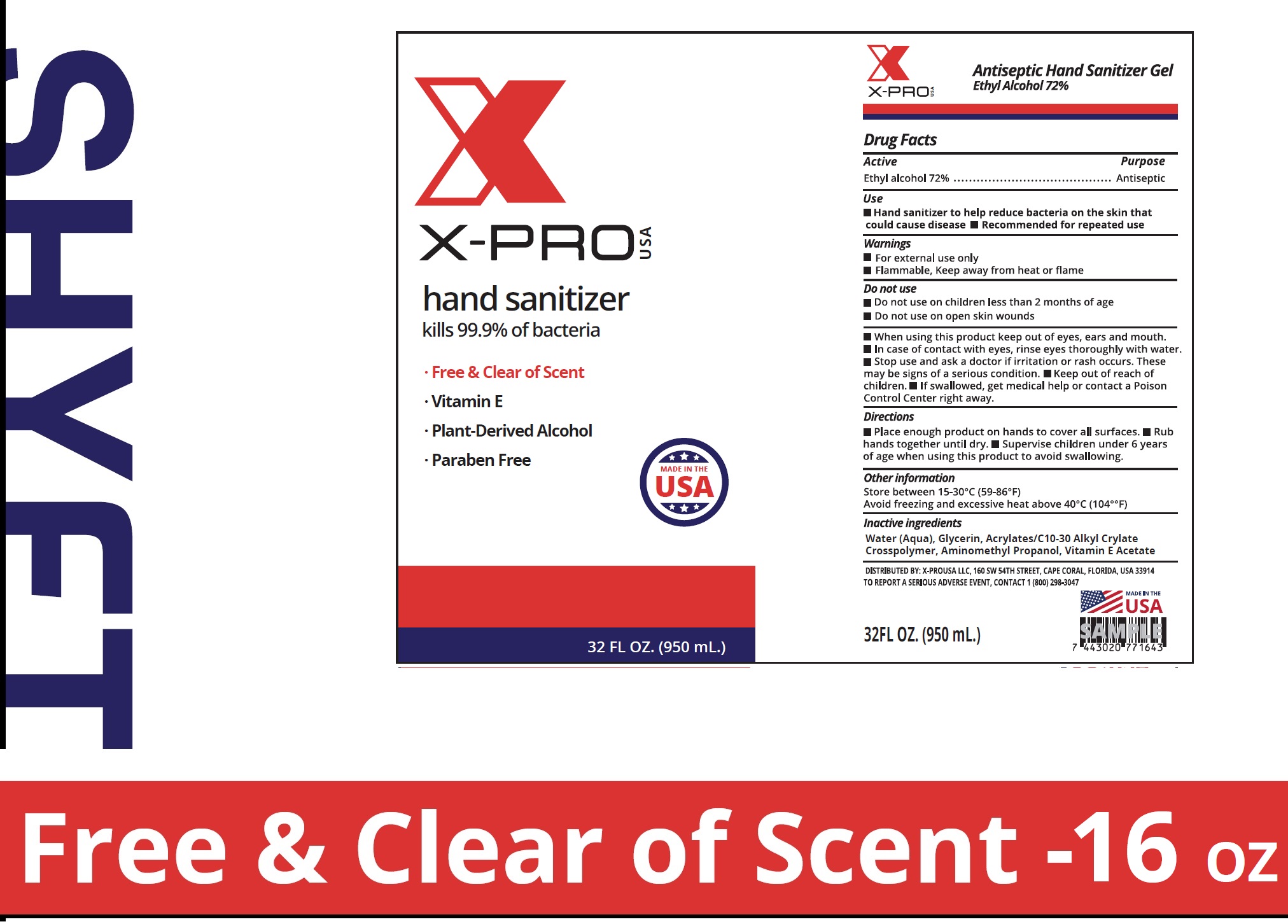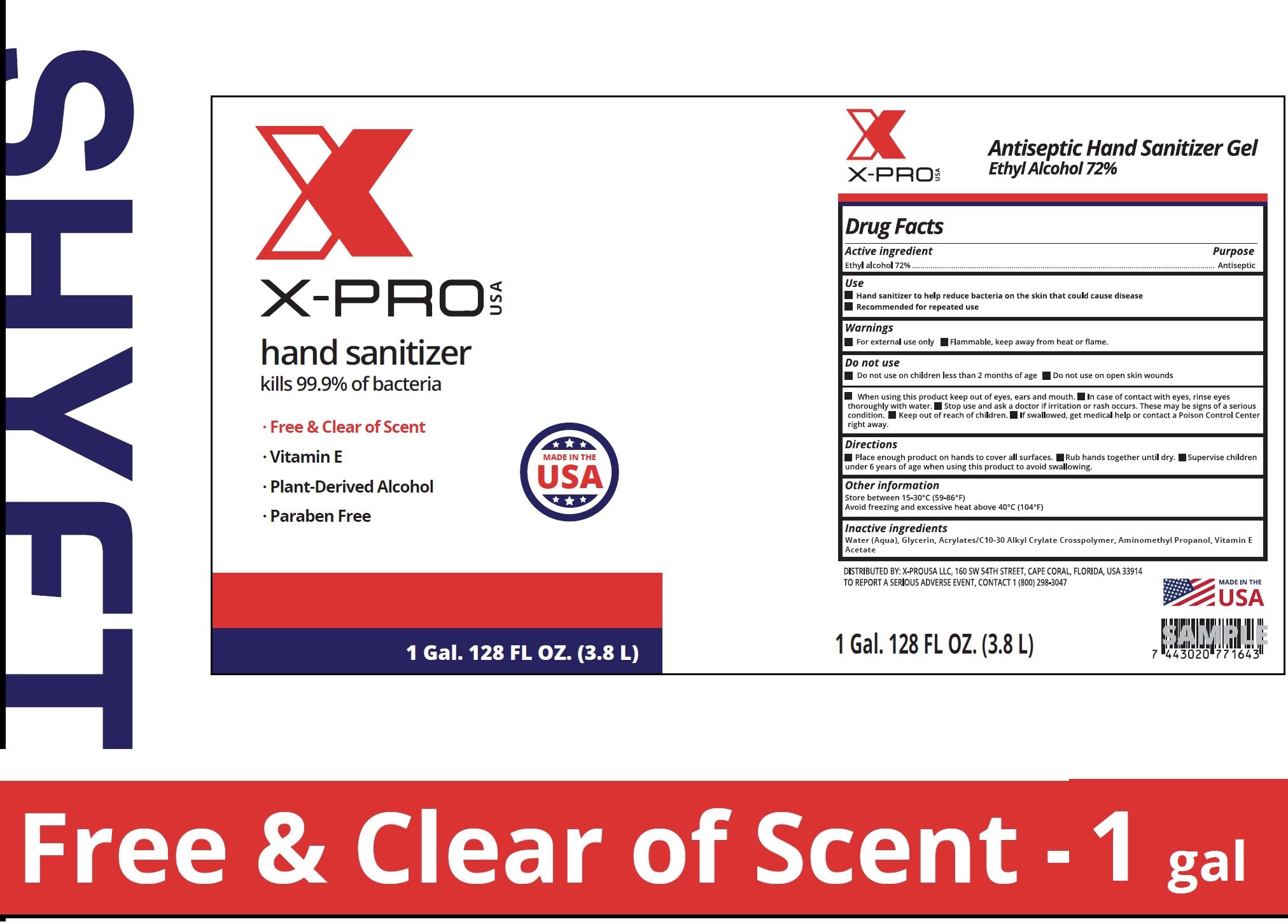 DRUG LABEL: X PROUSA Antiseptic Hand Sanitizer Gel
NDC: 79490-000 | Form: GEL
Manufacturer: X-PROUSA LLC
Category: otc | Type: HUMAN OTC DRUG LABEL
Date: 20200826

ACTIVE INGREDIENTS: ALCOHOL 0.72 mL/1 mL
INACTIVE INGREDIENTS: WATER; GLYCERIN; CARBOMER INTERPOLYMER TYPE A (ALLYL SUCROSE CROSSLINKED); AMINOMETHYLPROPANOL; .ALPHA.-TOCOPHEROL ACETATE

X-PROUSA Antiseptic Hand Sanitizer Gel

Active ingredient

Ethyl alcohol 72%

Purpose

Antiseptic

Use

- Hand sanitizer to help reduce bacteria on the skin that could cause disease
- Recommended for repeated use

Warnings

- For external use only
- Flammable, keep away from heat or flame

- Do not use on children less than 2 months of age
- Do not use on open skin wounds

When using this product

- keep out of eyes, ears and mouth.
- In case of contact with eyes, rinse eyes thoroughly with water.

Stop use and ask a doctor

if irritation or rash occurs. These may be signs of a serious condition.

Keep out of reach of children.

If swallowed, get medical help or contact a Poison Control Center right away.

Directions

- Place enough product on hands to cover all surfaces.
- Rub hands together until dry.
- Supervise children under 6 years of age when using this product to avoid swallowing.

Other information

Store between 15-30°C (59-86°F)
Avoid freezing and excessive heat above 40°C (104°F)

Inactive ingredients

Water (Aqua), Glycerin, Acrylates/C10-30 Alkyl Crylate Crosspolymer, Aminomethyl propanol, Vitamin E Acetate